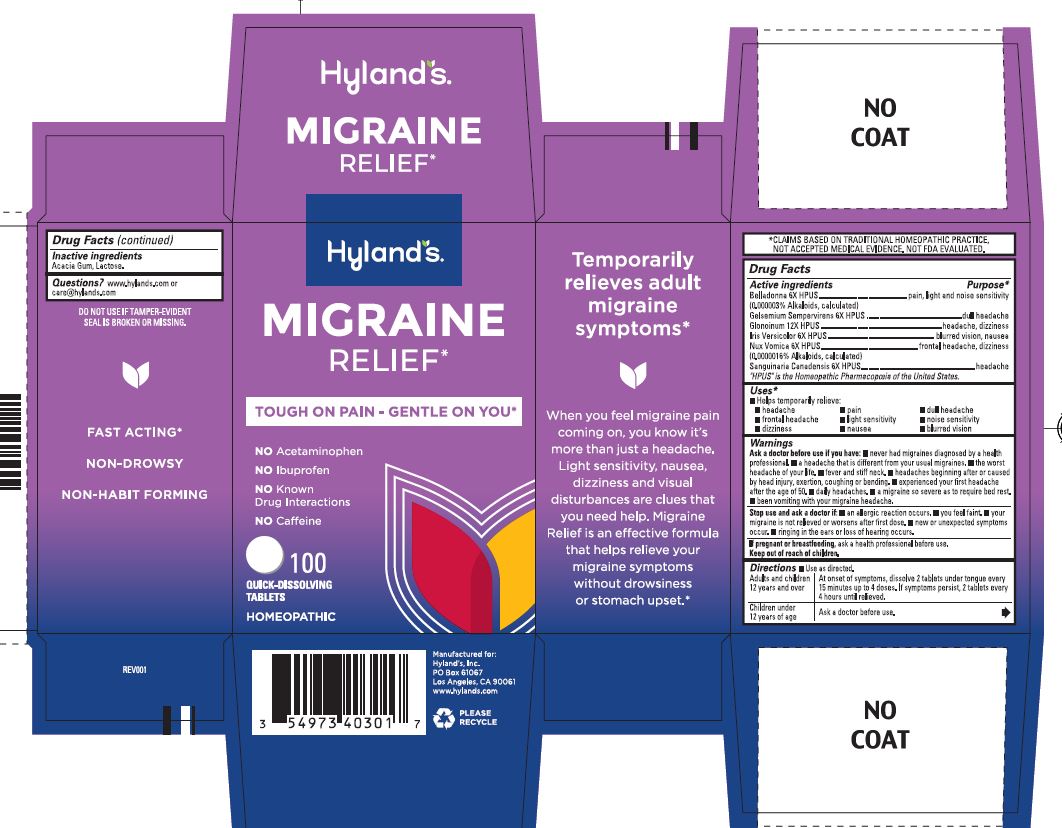 DRUG LABEL: Migraine Relief
NDC: 54973-4030 | Form: TABLET
Manufacturer: Hyland's Inc
Category: homeopathic | Type: HUMAN OTC DRUG LABEL
Date: 20250318

ACTIVE INGREDIENTS: NITROGLYCERIN 12 [hp_X]/1 1; GELSEMIUM SEMPERVIRENS ROOT 6 [hp_X]/1 1; SANGUINARIA CANADENSIS ROOT 6 [hp_X]/1 1; IRIS VERSICOLOR ROOT 6 [hp_X]/1 1; STRYCHNOS NUX-VOMICA SEED 6 [hp_X]/1 1; ATROPA BELLADONNA 6 [hp_X]/1 1
INACTIVE INGREDIENTS: ACACIA; LACTOSE MONOHYDRATE

Hyland's Migraine Relief

PURPOSE

Migraine Relief

Drug Facts

Active ingredients

Active ingredients | Purpose
Belladonna 6X HPUS; (0.0000003% Alkaloids, calculated) | pounding pain, light and noise sensitivity
Gelsemium 6X HPUS | dull headache
Glonoinum 12X HPUS | throbbing headache, dizziness
Iris Versicolor 6X HPUS | headache, blurred vision, nausea
Nux Vomica 6X HPUS; (0.0000016% Alkaloids, calculated) | frontal headache, dizziness
Sanguinaria Canadensis 6X HPUS | headache

"HPUS" indicates that the active ingredients are in the official Homeopathic

Pharmacopoeia of the United States.

Uses

■ Temporarily relieves symptoms of adult migraine headaches including:

■ throbbing headache ■ pounding pain ■ dull headache

■ frontal headache ■ light sensitivity ■ noise sensitivity

■ dizziness ■ nausea ■ blurred vision

Warnings

Ask a doctor before use if you have

■ never had migraines diagnosed by a health professional. ■ a headache that is different from your usual migraines. ■ the worst headache of your life. ■ fever and stiff neck. ■ headaches beginning after or caused by head injury, exertion, coughing or bending. ■ experienced your first headache after the age of 50. ■ daily headaches.  a migraine so severe as to require bed rest. ■ been vomiting with your migraine headache.

Stop use and ask a doctor if

■ an allergic reaction occurs. ■ you feel faint. ■ your migraine is not relieved or worsens after first dose. ■ new or unexpected symptoms occur. ■ ringing in the ears or loss of hearing occurs.

If pregnant or breastfeeding

Ask a health professional before use.

Directions

■ Use as directed.

Adults and children 12 years and over | At onset of symptoms, dissolve 2 tablets under tongue every 15 minutes up to 4 doses. If symptoms persist, 2 tablets every 4 hours until relieved.
Children under 12 years of age | Ask a doctor before use.

Drug Facts (continued)

Inactive ingredients

Acacia Gum, Lactose.

Questions?

www.hylands.com or care@hylands.com

Indications and Usage

Uses

removed extra bullets

PRINCIPAL DISPLAY PANEL

Hyland's

NATURALS

MIGRAINE

RELIEF*

TOUGH ON PAIN - GENTLE ON YOU

NO Acetaminophen

NO Ibruprofen

NO Known

Drug Interactions

NO Caffeine

100

QUICK - DISSOLVING

TABLETS

HOMEOPATHIC